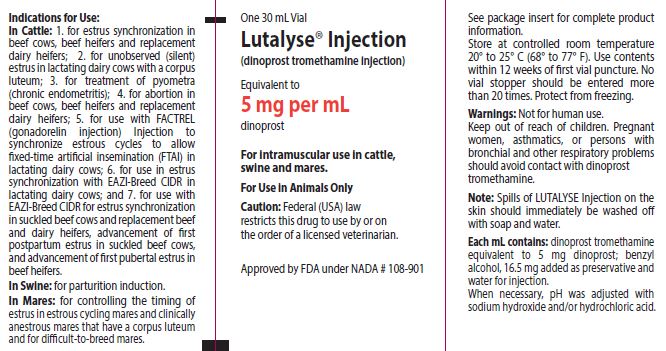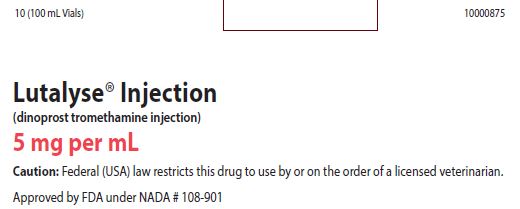 DRUG LABEL: Lutalyse
NDC: 54771-1327 | Form: INJECTION, SOLUTION
Manufacturer: Zoetis Inc.
Category: animal | Type: PRESCRIPTION ANIMAL DRUG LABEL
Date: 20240718

ACTIVE INGREDIENTS: DINOPROST TROMETHAMINE 5 mg/1 mL

Lutalyse® Injection

Caution

Federal (USA) law restricts this drug to use by or on the order of a licensed veterinarian.

(dinoprost tromethamine injection)

5 mg dinoprost/mL as dinoprost tromethamine

DESCRIPTION

LUTALYSE® Injection (5 mg dinoprost/mL) is a sterile solution containing the naturally occurring prostaglandin F2 alpha (dinoprost) as the tromethamine salt. Each mL contains dinoprost tromethamine equivalent to 5 mg dinoprost: also, benzyl alcohol, 16.5 mg added as preservative and water for injection.

When necessary, pH was adjusted with sodium hydroxide and/or hydrochloric acid. Dinoprost tromethamine is a white or slightly off-white crystalline powder that is readily soluble in water at room temperature in concentrations to at least 200 mg/mL.

INDICATIONS AND USAGE

Cattle

LUTALYSE Injection is indicated as a luteolytic agent. LUTALYSE Injection is effective only in those cattle having a corpus luteum, i.e., those which ovulated at least five days prior to treatment.

Future reproductive performance of animals that are not cycling will be unaffected by injection of LUTALYSE Injection.

• For estrus synchronization in beef cows, beef heifers and replacement dairy heifers

• For unobserved (silent) estrus in lactating dairy cows with a corpus luteum

• For treatment of pyometra (chronic endometritis) in cattle

• For abortion in beef cows, beef heifers and replacement dairy heifers

• For use with FACTREL (gonadorelin injection) Injection to synchronize estrous cycles to allow fixed-time artificial insemination (FTAI) in lactating dairy cows

• For use with EAZI-BREEDTM CIDR® (progesterone intravaginal insert) Cattle Insert for synchronization of estrus in lactating dairy cows

• For use with EAZI-BREEDTM CIDR® (progesterone intravaginal insert) Cattle Insert for synchronization of estrus in suckled beef cows and replacement beef and dairy heifers, advancement of first postpartum estrus in suckled beef cows, and advancement of first pubertal estrus in beef heifers

Swine

• For parturition induction in swine

Mares

• For controlling the timing of estrus in estrous cycling mares

• For difficult-to-breed mares (clinically anestrous mares that have a corpus luteum)

MANAGEMENT CONSIDERATIONS

Many factors contribute to success and failure of reproduction management, and these factors are important also when time of breeding is to be regulated with LUTALYSE Injection. Some of these factors are:

a. Cattle must be ready to breed—they must have a corpus luteum and be healthy;

b. Nutritional status must be adequate as this has a direct effect on conception and the initiation of estrus in heifers or return of estrous cycles in cows following calving;

c. Physical facilities must be adequate to allow cattle handling without being detrimental to the animal;

d. Estrus must be detected accurately if timed Al is not employed;

e. Semen of high fertility must be used;

f. Semen must be inseminated properly.

A successful breeding program can employ LUTALYSE Injection effectively, but a poorly managed breeding program will continue to be poor when LUTALYSE Injection is employed unless other management deficiencies are remedied first. Cattle expressing estrus following LUTALYSE Injection are receptive to breeding by a bull. Using bulls to breed large numbers of cattle in heat following LUTALYSE Injection will require proper management of bulls and cattle.

DOSAGE AND ADMINISTRATION

As with any multi-dose vial, practice aseptic techniques in withdrawing each dose to decrease the possibility of post-injection bacterial infections. Adequately clean and disinfect the vial stopper prior to entry with a sterile needle and syringe. Use only sterile needles, and use each needle only once.

No vial stopper should be entered more than 20 times. For this reason, the 100 mL bottle should only be used for cattle. The 30 mL bottle may be used for cattle, swine, or mares.

Cattle

1. For Estrus Synchronization in Beef Cows, Beef Heifers and Replacement Dairy Heifers. LUTALYSE Injection is used to control the timing of estrus and ovulation in estrous cycling cattle that have a corpus luteum. Inject a dose of 5 mL LUTALYSE Injection (25 mg dinoprost) intramuscularly either once or twice at a 10 to 12 day interval. With the single injection, cattle should be bred at the usual time relative to estrus. With the two injections cattle can be bred after the second injection either at the usual time relative to detected estrus or at about 80 hours after the second injection of LUTALYSE Injection. Estrus is expected to occur 1 to 5 days after injection if a corpus luteum was present. Cattle that do not become pregnant to breeding at estrus on days 1 to 5 after injection will be expected to return to estrus in about 18 to 24 days.

2. For Unobserved (Silent) Estrus in Lactating Dairy Cows with a Corpus Luteum. Inject a dose of 5 mL LUTALYSE Injection (25 mg dinoprost) intramuscularly. Breed cows as they are detected in estrus. If estrus has not been observed by 80 hours after injection, breed at 80 hours. If the cow returns to estrus, breed at the usual time relative to estrus.

3. For Treatment of Pyometra (chronic endometritis) in Cattle. Inject a dose of 5 mL LUTALYSE Injection (25 mg dinoprost) intramuscularly.

4. For Abortion in Beef Cows, Beef Heifers and Replacement Dairy Heifers. LUTALYSE Injection is indicated for its abortifacient effect in beef cows, beef heifers and replacement dairy heifers during the first 100 days of gestation. Inject a dose of 25 mg dinoprost (5 mL) intramuscularly. Cattle that abort will abort within 35 days of injection.

5. For use with FACTREL® (gonadorelin injection) Injection to synchronize estrous cycles to allow fixed-time artificial insemination (FTAI) in lactating dairy cows: Administer 2 to 4 mL FACTREL Injection (100-200 mcg gonadorelin) per cow as an intramuscular injection in a treatment regimen with the following framework:

• Administer the first dose of FACTREL Injection (2-4 mL) at Day 0

• Administer LUTALYSE (25 mg dinoprost, as dinoprost tromethamine) Injection by intramuscular injection 6-8 days after the first dose of FACTREL Injection.

• Administer a second dose of FACTREL Injection (2-4 mL) 30 to 72 hours after the LUTALYSE injection.

• Perform FTAI 0 to 24 hours after the second dose of FACTREL Injection, or inseminate cows on detected estrus using standard herd practices.

Below are three examples of treatment regimens for FTAI that fit within the dosage regimen framework described immediately above:

 | Example 1 | Example 2 | Example 3
Day 0; (Monday) | 1st FACTREL | 1st FACTREL | 1st FACTREL
Day 7; (the following Monday | LUTALYSE | LUTALYSE | LUTALYSE
Day 9 (Wednesday) | 2nd FACTREL + FTAI at 48 hours after LUTALYSE | 2nd FACTREL at 48 hours after LUTALYSE | 2nd FACTREL at 56 hours after LUTALYSE
Day 1; (Thursday) |  | FTAI 24 hours after 2nd FACTREL | FTAI 18 hours after 2nd FACTREL

6. For use with EAZI-BREED™ CIDR® (progesterone intravaginal insert) Cattle Insert for Synchronization of Estrus in Lactating Dairy Cows:

• Administer one EAZI-BREED CIDR Cattle Insert per animal and remove 7 days later (for example if administered on a Monday remove the following Monday).

• Administer 5 mL LUTALYSE Injection at the time of removal of the EAZI-BREED CIDR Cattle Insert.

• Observe animals for signs of estrus on Days 2 to 5 after removal of the EAZI-BREED CIDR Cattle Insert and inseminate animals found in estrus following normal herd practices.

7. For use with EAZI-BREED™ CIDR® (progesterone intravaginal insert) Cattle Insert for synchronization of estrus in suckled beef cows and replacement beef and dairy heifers, advancement of first postpartum estrus in suckled beef cows, and advancement of first pubertal estrus in beef heifers:

• Administer one EAZI-BREED CIDR Cattle Insert per animal for 7 days (for example, if administered on a Monday remove on the following Monday).

• Inject 5 mL LUTALYSE Injection (equivalent to 5 mg/mL dinoprost) 1 day prior to EAZIBREED CIDR Cattle Insert removal, on Day 6 of the 7 day administration period.

• Observe animals for signs of estrus on Days 1 to 3 after removal of the EAZI-BREED CIDR Cattle Insert and inseminate animals about 12 hours after onset of estrus.

Swine

For Parturition Induction in Swine: For intramuscular use for parturition induction in swine. LUTALYSE Injection is indicated for parturition induction in swine when injected within 3 days of normal predicted farrowing. The response to treatment varies by individual animals with a mean interval from administration of 2 mL LUTALYSE Injection (10 mg dinoprost) to parturition of approximately 30 hours. This can be employed to control the time of farrowing in sows and gilts in late gestation.
Management Considerations: Several factors must be considered for the successful use of LUTALYSE Injection for parturition induction in swine. The product must be administered at a relatively specific time (treatment earlier than 3 days prior to normal predicted farrowing may result in increased piglet mortality). It is important that adequate records be maintained on (1) the average length of gestation period for the animals on a specific location, and (2) the breeding and projected farrowing dates for each animal. This information is essential to determine the appropriate time for administration of LUTALYSE Injection.

Mares

LUTALYSE Injection is indicated for its luteolytic effect in mares. Administer a single intramuscular injection of 1 mg per 100 lbs (45.5 kg) body weight which is usually 1 mL to 2 mL LUTALYSE Injection. This luteolytic effect can be utilized to control the timing of estrus in estrous cycling and clinically anestrous mares that have a corpus luteum in the following circumstances:
1. Controlling Time of Estrus of Estrous Cycling Mares: Mares treated with LUTALYSE Injection during diestrus (4 or more days after ovulation) will return to estrus within 2 to 4 days in most cases and ovulate 8 to 12 days after treatment. This procedure may be utilized as an aid to scheduling the use of stallions.
2. Difficult-to-Breed Mares: In extended diestrus there is failure to exhibit regular estrous cycles which is different from true anestrus. Many mares described as anestrus during the breeding season have serum progesterone levels consistent with the presence of a functional corpus luteum. A proportion of “barren”, maiden, and lactating mares do not exhibit regular estrous cycles and may be in extended diestrus. Following abortion, early fetal death and resorption, or as a result of “pseudopregnancy”, there may be serum progesterone levels consistent with a functional corpus luteum. Treatment of such mares with LUTALYSE Injection usually results in regression of the corpus luteum followed by estrus and/or ovulation. Treatment of “anestrous” mares which abort subsequent to 36 days of pregnancy may not result in return to estrus due to presence of functional endometrial cups.

WARNINGS AND PRECAUTIONS

User Safety: Not for human use. Keep out of the reach of children. Women of childbearing age, asthmatics, and persons with bronchial and other respiratory problems should exercise extreme caution when handling this product. In the early stages, women may be unaware of their pregnancies. Dinoprost tromethamine is readily absorbed through the skin and can cause abortion and/or bronchiospasms. Accidental spillage on the skin should be washed off immediately with soap and water.

Residue Warnings: No milk discard or preslaughter drug withdrawal period is required for labeled uses in cattle. No preslaughter drug withdrawal period is required for labeled uses in swine. Use of this product in excess of the approved dose may result in drug residues. Do not use in horses intended for human consumption.

Animal Safety Warnings: Severe localized clostridial infections associated with injection of LUTALYSE Injection have been reported. In rare instances, such infections have resulted in death.

Aggressive antibiotic therapy should be employed at the first sign of infection at the injection site whether localized or diffuse. Do not administer intravenously (IV) as this route may potentiate adverse reactions. Non-steroidal anti-inflammatory drugs may inhibit prostaglandin synthesis; therefore this class of drugs should not be administered concurrently. Do not administer to pregnant cattle, unless abortion is desired. Cattle administered a progestin would be expected to have a reduced response to LUTALYSE Injection. Do not administer to sows and/or gilts prior to 3 days of normal predicted farrowing as an increased number of stillbirths and postnatal mortality may result. In mares, LUTALYSE Injection is ineffective when administered prior to day-5 after ovulation.

Mare pregnancy status should be determined prior to treatment since LUTALYSE Injection has been reported to induce abortion and parturition when sufficient doses were administered. Mares should not be treated if they suffer from either acute or subacute disorders of the vascular system, gastrointestinal tract, respiratory system, or reproductive tract.

ADVERSE REACTIONS

Cattle: Limited salivation has been reported in some instances.

Swine: The most frequently observed side effects were erythema and pruritus, slight incoordination, nesting behavior, itching, urination, defecation, abdominal muscle spasms, tail movements, hyperpnea or dyspnea, increased vocalization, salivation, and at the 100 mg (10x) dose only, possible vomiting. These side effects are transitory, lasting from 10 minutes to 3 hours, and were not detrimental to the health of the animal.

Mares: The most frequently observed side effects are sweating and decreased rectal temperature. However, these have been transient in all cases observed and have not been detrimental to the animal.

Other reactions seen have been increase in heart rate, increase in respiration rate, some abdominal discomfort, locomotor incoordination, and lying down. These effects are usually seen within 15 minutes of injection and disappear within one hour. Mares usually continue to eat during the period of expression of side effects. One anaphylactic reaction of several hundred mares treated with LUTALYSE Injection was reported but was not confirmed.

CONTACT INFORMATION
For a copy of the Safety Data Sheet or to report adverse reactions, call Zoetis Inc. at 1-888-963-8471. For additional information about adverse drug experience reporting for animal drugs, contact FDA at 1-888-FDA-VETS or www.fda.gov/reportanimalae.

CLINICAL PHARMACOLOGY

General Biologic Activity: Prostaglandins occur in nearly all mammalian tissues. Prostaglandins, especially PGE’s and PGF’s, have been shown, in certain species, to 1) increase at time of parturition in amniotic fluid, maternal placenta, myometrium, and blood, 2) stimulate myometrial activity, and 3) to induce either abortion or parturition. Prostaglandins, especially PGF2α, have been shown to 1) increase in the uterus and blood to levels similar to levels achieved by exogenous administration which elicited luteolysis, 2) be capable of crossing from the uterine vein to the ovarian artery (sheep), 3) be related to IUD induced luteal regression (sheep), and 4) be capable of regressing the corpus luteum of most mammalian species studied to date. Prostaglandins have been reported to result in release of pituitary tropic hormones. Data suggest prostaglandins, especially PGE’s and PGF’s, may be involved in the process of ovulation and gamete transport. Also PGF2α has been reported to cause increase in blood pressure, bronchoconstriction, and smooth muscle stimulation in certain species.

Metabolism: A number of metabolism studies have been done in laboratory animals. The metabolism of tritium labeled dinoprost (3H PGF2 alpha) in the rat and in the monkey was similar.

Although quantitative differences were observed, qualitatively similar metabolites were produced. A study demonstrated that equimolar doses of 3H PGF2 alpha Tham and 3H PGF2 alpha free acid administered intravenously to rats demonstrated no significant differences in blood concentration of dinoprost. An interesting observation in the above study was that the radioactive dose of 3H PGF2 alpha rapidly distributed in tissues and dissipated in tissues with almost the same curve as it did in the serum. The half-life of dinoprost in bovine blood has been reported to be on the order of minutes. A complete study on the distribution of decline of 3H PGF2 alpha Tham in the tissue of rats was well correlated with the work done in the cow. Cattle serum collected during 24 hours after doses of 0 to 250 mg dinoprost have been assayed by RIA for dinoprost and the 15-keto metabolites. These data support previous reports that dinoprost has a halflife of minutes. Dinoprost is a natural prostaglandin. All systems associated with dinoprost metabolism exist in the body; therefore, no new metabolic, transport, excretory, binding or other systems need be established by the body to metabolize injected dinoprost.

TARGET ANIMAL SAFETY

Laboratory Animals

Dinoprost was non-teratogenic in rats when administered orally at 1.25, 3.2, 10.0 and 20.0 mg dinoprost/kg/day from day 6th-15th of gestation or when administered subcutaneously at 0.5 and 1.0 mg/ kg/day on gestation days 6, 7 and 8 or 9, 10 and 11 or 12, 13 and 14. Dinoprost was non-teratogenic in the rabbit when administered either subcutaneously at doses of 0.5 and 1.0 mg dinoprost/kg/day on gestation days 6, 7 and 8 or 9, 10 and 11 or 12, 13 and 14 or 15, 16 and 17 or orally at doses of 0.01, 0.1 and 1.0 mg dinoprost/ kg/day on days 6-18 or 5.0 mg/kg/day on days 8-18 of gestation. A slight and marked embryo lethal effect was observed in dams given 1.0 and 5.0 mg dinoprost/kg/ day respectively. This was due to the expected luteolytic properties of the drug.

A 14-day continuous intravenous infusion study in rats at 20 mg PGF2α per kg body weight indicated prostaglandins of the F series could induce bone deposition. However, such bone changes were not observed in monkeys similarly administered LUTALYSE Injection at 15 mg dinoprost per kg body weight for 14 days.

Cattle

In cattle, evaluation was made of clinical observations, clinical chemistry, hematology, urinalysis,organ weights, and gross plus microscopic measurements following treatment with various doses up to 250 mg dinoprost administered twice intramuscularly at a 10 day interval or doses of 25 mg administered daily for 10 days. There was no unequivocal effect of dinoprost on the hematology or clinical chemistry parameters measured. Clinically, a slight transitory increase in heart rate was detected. Rectal temperature was elevated about 1.5˚ F through the 6th hour after injection with 250 mg dinoprost, but had returned to baseline at 24 hours after injection. No dinoprost associated gross lesions were detected. There was no evidence of toxicological effects. Thus, dinoprost had a safety factor of at least 10X on injection (25 mg luteolytic dose vs. 250 mg safe dose), based on studies conducted with cattle. At luteolytic doses, dinoprost had no effect on progeny. If given to a pregnant cow, it may cause abortion; the dose required for abortion varies considerably with the stage of gestation. Induction of abortion in feedlot cattle at stages of gestation up to 100 days of gestation did not result in dystocia, retained placenta or death of heifers in the field studies. The smallness of the fetus at this early stage of gestation should not lead to complications at abortion. However, induction of parturition or abortion with any exogenous compound may precipitate dystocia, fetal death, retained placenta and/or metritis, especially at latter stages of gestation.

Swine

In pigs, evaluation was made of clinical observations, food consumption, clinical pathologic determinations, body weight changes, urinalysis, organ weights, and gross and microscopic observations following treatment with single doses of 10, 30, 50 and 100 mg dinoprost administered intramuscularly. The results indicated no treatment related effects from dinoprost treatment that were deleterious to the health of the animals or to their offspring.

Mares

Dinoprost tromethamine was administered to adult mares (weighing 320 to 485 kg; 2 to 20 yearsold), at the rates of 0, 100, 200, 400, and 800 mg per mare per day for 8 days. Route of administration for each dose group was both intramuscularly (2 mares) and subcutaneously (2 mares). Changes were detected in all treated groups for clinical (reduced sensitivity to pain; locomotor incoordination; hypergastromotility; sweating; hyperthermia; labored respiration), blood chemistry (elevated cholesterol, total bilirubin, LDH, and glucose), and hematology (decreased eosinophils; increased hemoglobin, hematocrit, and erythrocytes) measurements. The effects in the 100 mg dose, and to a lesser extent, the 200 mg dose groups were transient in nature, lasting for a few minutes to several hours. Mares did not appear to sustain adverse effects following termination of the side effects.

Mares treated with either 400 mg or 800 mg exhibited more profound symptoms. The excessive hyperstimulation of the gastrointestinal tract caused a protracted diarrhea, slight electrolyte imbalance (decreased sodium and potassium), dehydration, gastrointestinal irritation, and slight liver malfunction (elevated SGOT, SGPT at 800 mg only). Heart rate was increased but pH of the urine was decreased. Other measurements evaluated in the study remained within normal limits. No mortality occurred in any of the groups. No apparent differences were observed between the intramuscular and subcutaneous routes of administration. Luteolytic doses of dinoprost tromethamine are on the order of 5 to 10 mg administered on one day, therefore, LUTALYSE Injection was demonstrated to have a wide margin of safety. Thus, the 100 mg dose gave a safety margin of 10 to 20X for a single injection or 80 to 160X for the 8 daily injections. Additional studies investigated the effects in the mare of single intramuscular doses of 0, 0.25, 1.0, 2.5, 3.0, 5.0, and 10.0 mg dinoprost tromethamine. Heart rate, respiration rate, rectal temperature, and sweating were measured at 0, 0.25, 0.50, 0.75, 1.0, 1.5, 2.0, 3.0, 4.0, 5.0, and 6.0 hr. after injection. Neither heart rate nor respiration rates were significantly altered (P > 0.05) when compared to contemporary control values. Sweating was observed for 0 of 9, 2 of 9, 7 of 9, 9 of 9, and 8 of 9 mares injected with 0.25, 1.0, 2.5, 3.0, 5.0, or 10.0 mg dinoprost tromethamine, respectively. Sweating was temporary in all cases and was mild for doses of 3.0 mg or less but was extensive (beads of sweat over the entire body and dripping) for the 10 mg dose. Sweating after the 5.0 mg dose was intermediate between that seen for mares treated with 3.0 and 10.0 mg. Sweating began within 15 minutes after injection and ceased by 45 to 60 minutes after injection. Rectal temperature was decreased during the interval 0.5 until 1.0, 3 to 4, or 5 hours after injection for 0.25 and 1.0 mg, 2.5 and 3.0, or 5.0 and 10.0 mg dose groups, respectively. Average rectal temperature during the periods of decreased temperature was on the orderof 97.5 to 99.6, with the greatest decreases observed in the 10 mg dose group.

EFFECTIVESS

Cattle:

For Treatment of Pyometra (chronic endometritis) in Cattle: In studies conducted with LUTALYSE Injection, pyometra was defined as presence of a corpus luteum in the ovary and uterine horns containing fluid but not a conceptus based on palpation per rectum. Return to normal was defined as evacuation of fluid and return of the uterine horn size to 40mm or less based on palpation per rectum at 14 and 28 days. Most cattle that recovered in response to LUTALYSE Injection recovered within 14 days after injection. After 14 days, recovery rate of treated cattle was no different than that of non-treated cattle.

For Abortion in Beef Cows, Beef Heifers and Replacement Dairy Heifers: Commercial cattle were palpated per rectum for pregnancy in six feedlots. The percent of pregnant cattle in each feedlot less than 100 days of gestation ranged between 26 and 84; 80% or more of the pregnant cattle were less than 150 days of gestation. The abortion rates following injection of LUTALYSE Injection increased with increasing doses up to about 25 mg. As examples, the abortion rates, over 7 feedlots on the dose titration study, were 22%, 50%, 71%, 90% and 78% for cattle up to 100 days of gestation when injected IM with LUTALYSE Injection doses of 0,1 (5 mg), 2 (10 mg), 4 (20 mg) and 8 (40 mg) mL, respectively. The statistical predicted relative abortion rate based on the dose titration data, was about 93% for the 5 mL (25 mg) LUTALYSE Injection dose for cattle injected up to 100 days of gestation.

For use with FACTREL® (gonadorelin injection) Injection to synchronize estrous cycles to allow fixedtime artificial insemination (FTAI) in lactating dairy cows: For a full description of the studies conducted for the use of FACTREL Injection and LUTALYSE Injection, please refer to the labeling for FACTREL Injection.

Mares: For Difficult-to-Breed Mares: In one study with 122 Standardbred and Thoroughbred mares in clinical anestrus for an average of 58 days and treated during the breeding season, behavioral estrus was detected in 81 percent at an average time of 3.7 days after injection with 5 mg LUTALYSE Injection; ovulation occurred an average of 7.0 days after treatment. Of those mares bred, 59% were pregnant following an average of 1.4 services during that estrus.

HOW SUPPLIED

LUTALYSE Injection is available in 30 and 100 mL vials.

STORAGE CONDITIONS

Store at controlled room temperature 20° to 25°C (68° to 77°F).
Use contents within 12 weeks of first vial puncture.
Protect from freezing.

Approved by FDA under NADA # 108-901
zoetis
Distributed by:
Zoetis Inc.
Kalamazoo, MI 49007
Revised: September 2021
40034684